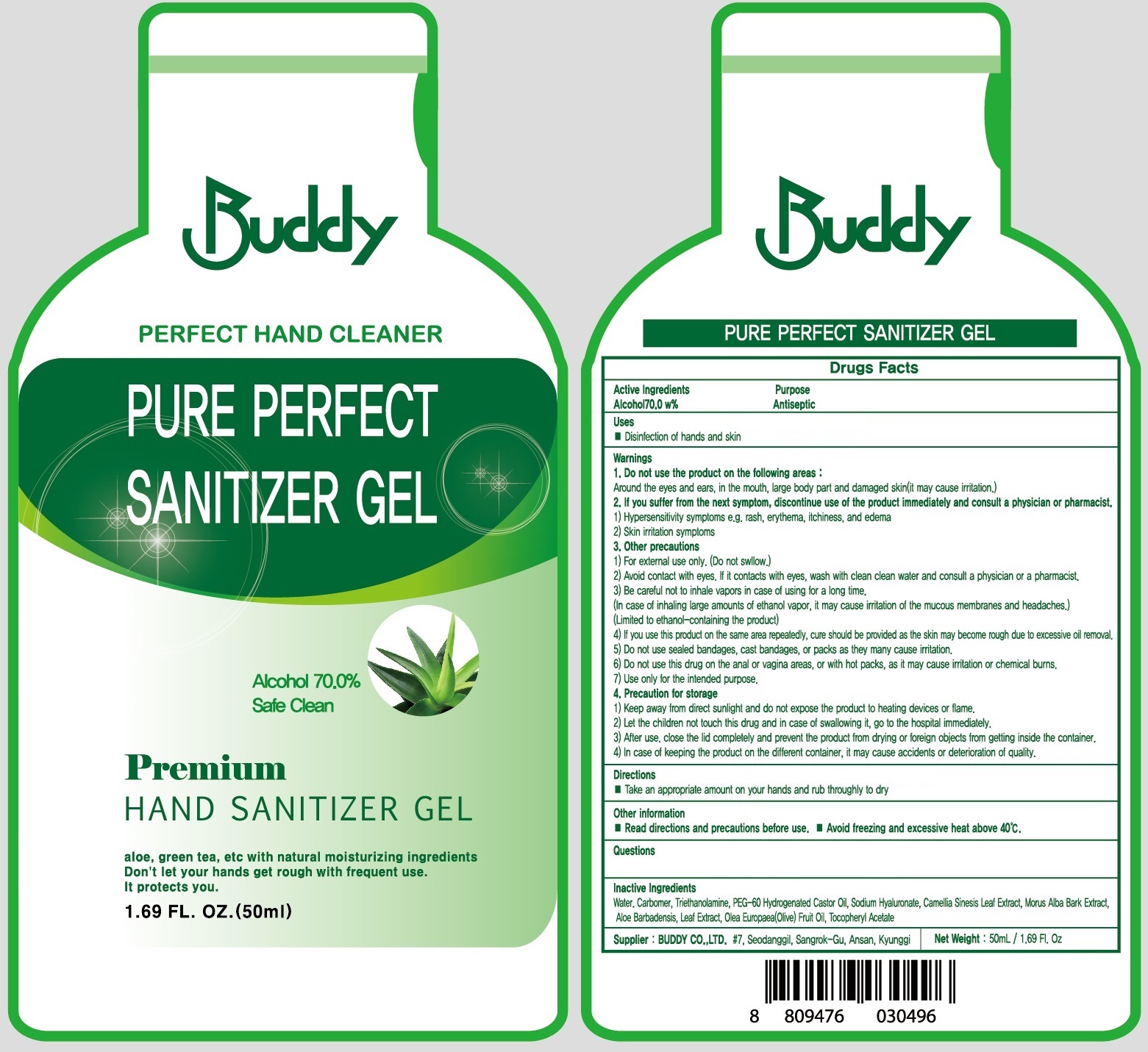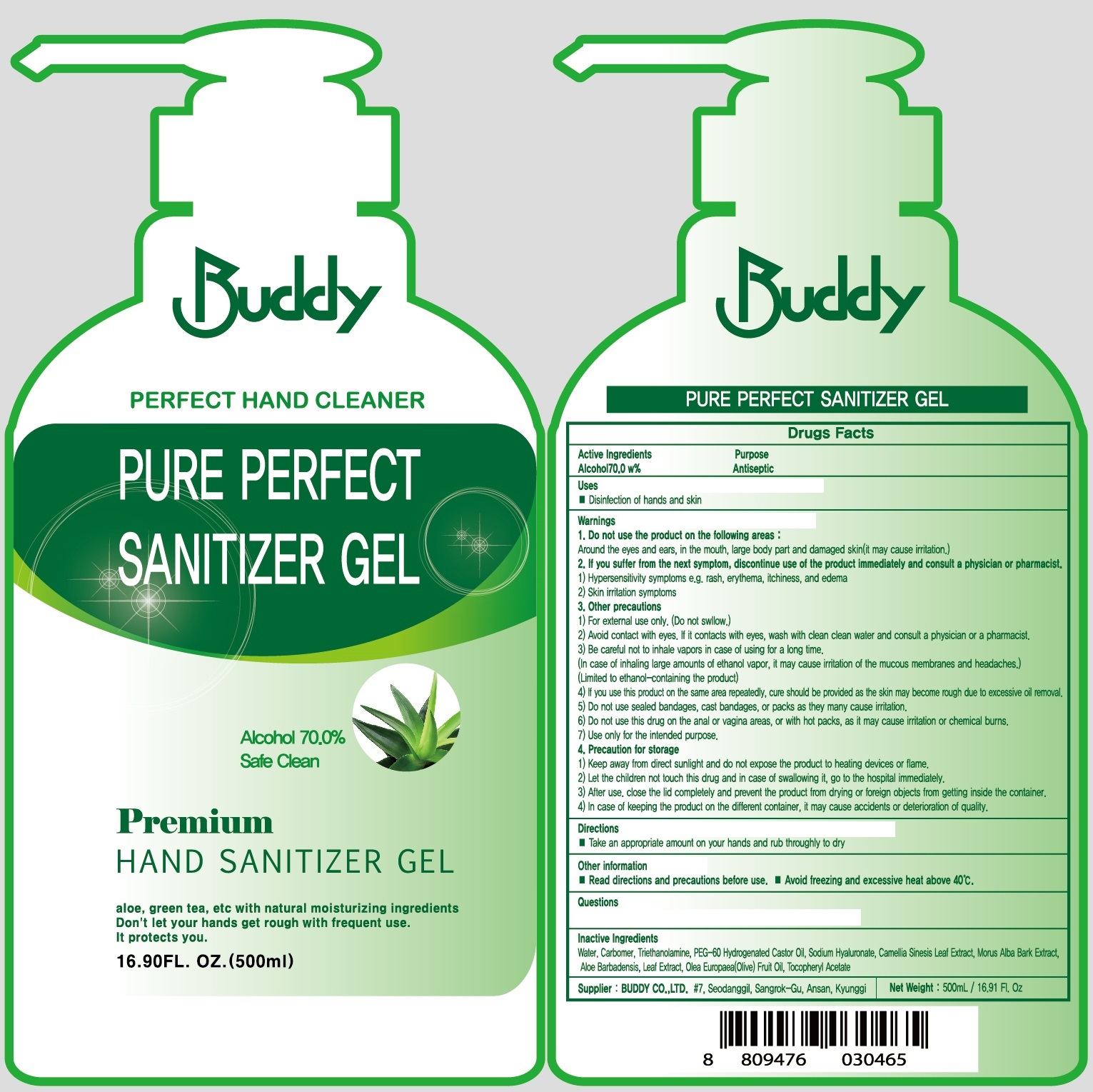 DRUG LABEL: PURE PERFECT SANITIZER
NDC: 74716-010 | Form: GEL
Manufacturer: Buddy Co., Ltd.
Category: otc | Type: HUMAN OTC DRUG LABEL
Date: 20200413

ACTIVE INGREDIENTS: ALCOHOL 70 g/100 mL
INACTIVE INGREDIENTS: Water; CARBOMER HOMOPOLYMER, UNSPECIFIED TYPE; TROLAMINE; PEG-60 Hydrogenated Castor Oil; HYALURONATE SODIUM; GREEN TEA LEAF; MORUS ALBA BARK; ALOE VERA LEAF; OLIVE OIL; .ALPHA.-TOCOPHEROL ACETATE

ACTIVE INGREDIENT

Active ingredients: ALCOHOL 70.0 w%

INACTIVE INGREDIENT

Inactive Ingredients:

Water, Carbomer, Triethanolamine, PEG-60 Hydrogenated Castor Oil, Sodium Hyaluronate, Camellia Sinesis Leaf Extract, Morus Alba Bark Extract, Aloe Barbadensis, Leaf Extract, Olea Europaea(Olive) Fruit Oil, Tocopheryl Acetate

PURPOSE

Purpose: Antiseptic

WARNINGS

1. Do not use the product on the following areas :
Around the eyes and ears, in the mouth, large body part and damaged skin(it may cause irritation.)
2. If you suffer from the next symptom, discontinue use of the product immediately and consult a physician or pharmacist.
1) Hypersensitivity symptoms e.g. rash, erythema, itchiness, and edema
2) Skin irritation symptoms

3. Other precautions
1) For external use only. (Do not swllow.)
2) Avoid contact with eyes. If it contacts with eyes, wash with clean clean water and consult a physician or a pharmacist.
3) Be careful not to inhale vapors in case of using for a long time.
(In case of inhaling large amounts of ethanol vapor, it may cause irritation of the mucous membranes and headaches.)
(Limited to ethanol-containing the product)
4) If you use this product on the same area repeatedly, cure should be provided as the skin may become rough due to excessive oil removal.
5) Do not use sealed bandages, cast bandages, or packs as they many cause irritation.
6) Do not use this drug on the anal or vagina areas, or with hot packs, as it may cause irritation or chemical burns.
7) Use only for the intended purpose.

4. Precaution for storage
1) Keep away from direct sunlight and do not expose the product to heating devices or flame.
2) Let the children not touch this drug and in case of swallowing it, go to the hospital immediately.
3) After use. close the lid completely and prevent the product from drying or foreign objects from getting inside the container.
4) In case of keeping the product on the different container, it may cause accidents or deterioration of quality.

KEEP OUT OF REACH OF CHILDREN

Uses

Disinfection of hands and skin

Directions

Spray an appropriate amount on your hands and rub thoroughly to dry.

Other information

■ Read directions and precautions before use.
■ Avoid freezing and excessive heat above 40℃.